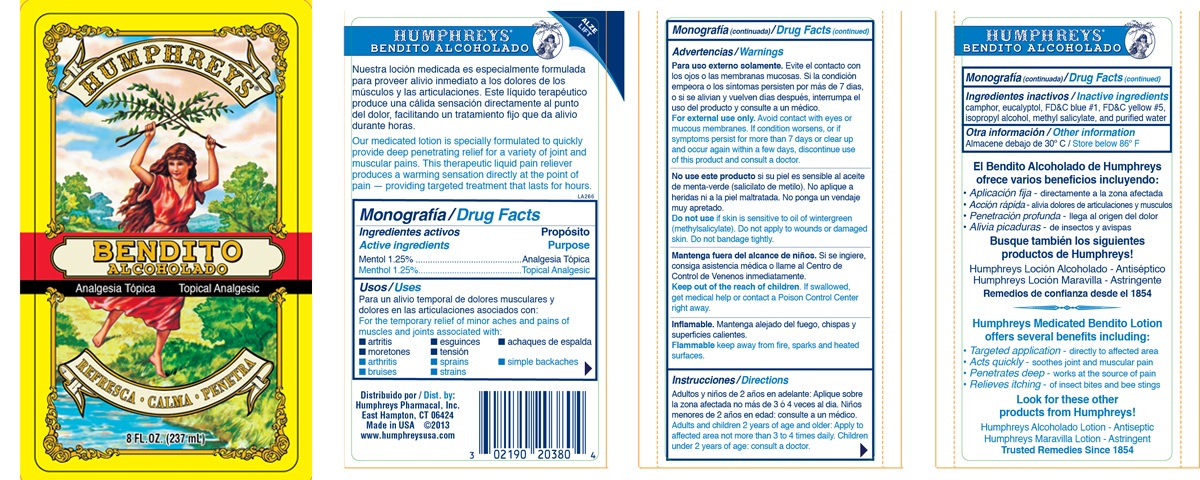 DRUG LABEL: Humphreys Bendito Alcoholado
NDC: 0219-0203 | Form: LIQUID
Manufacturer: Humphreys Pharmacal, Incorporated
Category: otc | Type: HUMAN OTC DRUG LABEL
Date: 20241209

ACTIVE INGREDIENTS: MENTHOL, UNSPECIFIED FORM 12.5 mg/1 mL
INACTIVE INGREDIENTS: CAMPHOR (SYNTHETIC); EUCALYPTOL; FD&C BLUE NO. 1; FD&C YELLOW NO. 5; ISOPROPYL ALCOHOL; METHYL SALICYLATE; WATER

Monografía / Drug Facts

Ingrediente activo / Active ingredients

Mentol / Menthol 1.25%

Propósito / Purpose

Analgesia Tópica / Topical Anaglesic

Usos / Uses

Para un alivio temporal de dolores musculares y dolores en las articulaciones asociados con:

- artritis
- moretones
- esguinces
- tensión
- achaques de espalda

For the temporary relief of minor aches and pains of muscles and joints associated with:

- arthritis
- bruises
- sprains
- strains
- simple backache

Advertencias / Warnings

Para uso externo solamente. Evite el contacto con los ojos o las membranas mucosas. Si la condición empeora o los síntomas persisten por más de 7 dias, o si se aliviany retoman días después, interrumpa el uso del producto y consulte a un médico.
For external use only. Avoid contact with eyes or mucous membranes. If condition worsens, or if symptoms persist for more than 7 days or clear up and occur again within a few days, discontinue use of this product and consult a doctor.

DO NOT USE

No use este producto si su piel es sensible al aceite de menta-verde (salicilato de metilo). No aplique a heridas ni a la piel maltratada. No ponga un vendaje muy apretado.
Do not use if skin is sensitive to oil of wintergreen (methylsalicylate). Do not apply to wounds or damaged skin. Do not bandage tightly.

KEEP OUT OF REACH OF CHILDREN

Mantenga fuera del alcance de niños. Si se ingiere, consiga asistencia médica o llame al Centro de Control de Venenos inmediatamente.
Keep out of the reach of children. If swallowed,get medical help or contact a Poison Control Center right away

USER SAFETY WARNINGS

Inflamable. Mantenga alejado del fuego, chispas y superficies calientes.
Flammable keep away from fire, sparks and heated surfaces.

Instrucciones / Directions

Adultos y niños de 2 años en adelante: Aplique sobre la zona afectada no más de 3 ó 4 veces al dia. Niños menores de 2 años en edad: consulte a un médico.
Adults and children 2 years of age and older: Apply to affected area not more than 3 to 4 times daily. Children under 2 years of age: consult a doctor.

Ingredientes inactivos / Inactive ingredients

camphor, eucalyptol, FDC blue #1, FDC yellow #5, isopropyl alcohol, methyl salicylate, and purified water

Otra información / Other information

Almacene debajo de 30C / Store below 86F

QUESTIONS

Distribuido por / Dist. by:
Humphreys Pharmacal, Inc.
East Hampton, CT 06424
Made in USA

www.humphreysusa.com

PACKAGE LABEL

The labels shown below represent a sample of that currently in use. Additional packaging may also be available.

HUMPHREYS

BENDITO
ALCOHOLADO

Analgesia Tópica / Topical Anaglesic

REFRESCA - CALMA - PENETRA